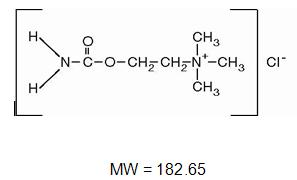 DRUG LABEL: Unknown
Manufacturer: Novartis Ophthalmics
Category: prescription | Type: HUMAN PRESCRIPTION DRUG LABELING
Date: 20060919

Carbastat®

Carbastat®

(CARBACHOL INTRAOCULAR SOLUTION, USP) 0.01%

DESCRIPTION

CARBASTAT® (Carbachol Intraocular Solution, USP) 0.01% is a sterile balanced salt solution of carbachol for intraocular injection. The active ingredient is represented by the structural formula:

Established name: Carbachol

Chemical name: Ethanaminium, 2-[(aminocarbonyl)oxy]-N,N,N -trimethyl-, chloride.

Each mL contains: Active: Carbachol 0.01%.

Inactive: Sodium chloride 0.64%, potassium chloride 0.075%, calcium chloride dihydrate 0.048%, magnesium chloride hexahydrate 0.03%, sodium acetate trihydrate 0.39%, sodium citrate dihydrate 0.17%, sodium hydroxide and/or hydrochloric acid to adjust pH (5.0-7.5) and water for injection USP.

CLINICAL PHARMACOLOGY

Carbachol is a potent cholinergic (parasympathomimetic) agent which produces constriction of the iris and ciliary body resulting in reduction in intraocular pressure. The exact mechanism by which carbachol lowers intraocular pressure is not precisely known.

INDICATIONS AND USAGE

Intraocular use for obtaining miosis during surgery. In addition, Carbastat® (Carbachol Intraocular Solution USP) reduces the intensity of intraocular pressure elevation in the first 24 hours after cataract surgery.

CONTRAINDICATIONS

Should not be used in those persons showing hypersensitivity to any of the components of this preparation.

WARNINGS

For single-dose intraocular use only. Discard unused portion. Intraocular carbachol 0.01% should be used with caution in patients with acute cardiac failure, bronchial asthma, peptic ulcer, hyperthyroidism, G.I. spasm, urinary tract obstruction and Parkinson's disease.

PRECAUTIONS

Carcinogenesis

Studies in animals to evaluate the carcinogenic potential have not been conducted.

Pregnancy: Category C.

There are no adequate and well controlled studies in pregnant women. Carbastat® should be used during pregnancy only if the potential benefit justifies the potential risk to the fetus.

Nursing Mothers

It is not known if this medication is excreted in breast milk. Exercise caution when administering to a nursing woman.

Pediatric Use

Safety and efficacy in pediatric patients have not been established.

ADVERSE REACTIONS

Ocular

Corneal clouding, persistent bullous keratopathy, retinal detachment and postoperative iritis following cataract extraction have been reported.

Systemic

Side effects such as flushing, sweating, epigastric distress, abdominal cramps, tightness in urinary bladder, and headache have been reported with topical or systemic application of carbachol.

DOSAGE AND ADMINISTRATION

Aseptically remove the sterile vial from the blister package by peeling the backing paper and dropping the vial onto a sterile tray. Withdraw the contents into a dry sterile syringe, and replace the needle with an atraumatic cannula prior to intraocular irrigation. No more than one-half milliliter should be gently instilled into the anterior chamber for the production of satisfactory miosis. It may be instilled before or after securing sutures. Miosis is usually maximal within two to five minutes after application.

HOW SUPPLIED

CARBASTAT (Carbachol Intraocular Solution, USP) 0.01%

1.5 mL sterile glass vials in cartons of 12 (12 x 1.5 mL)

NDC 58768-735-12

Store at controlled room temperature 15°-30°C (59°-86°F).

Rx only

Manufactured by OMJ Pharmaceuticals, Inc.,

San Germán, P.R. 00683

for Novartis Ophthalmics

Duluth, GA 30097

5007-D

March, 2001